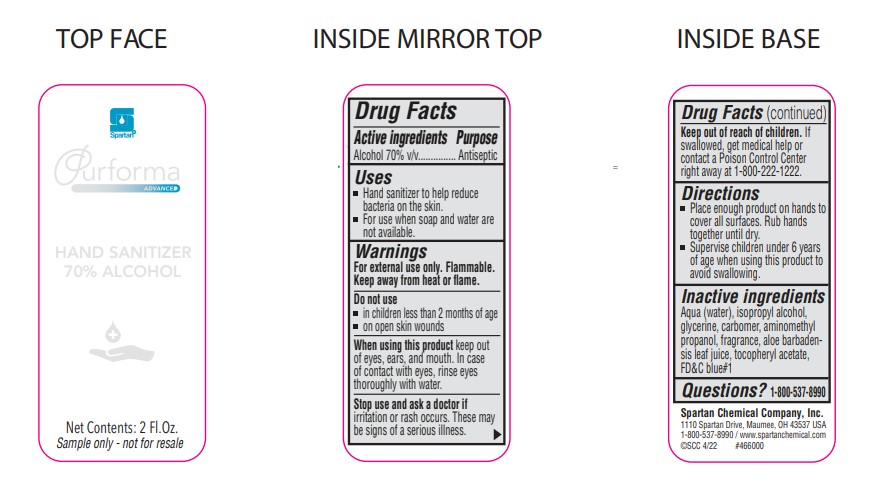 DRUG LABEL: Purforma Advanced Hand Sanitizer 70% Alcohol
NDC: 64009-660 | Form: SOAP
Manufacturer: Spartan Chemical Company, Inc.
Category: otc | Type: HUMAN OTC DRUG LABEL
Date: 20251006

ACTIVE INGREDIENTS: ALCOHOL 70 mL/100 mL
INACTIVE INGREDIENTS: GLYCERIN; CARBOMER 980; .ALPHA.-TOCOPHEROL ACETATE; WATER; ALOE; AMINOMETHYL PROPANEDIOL; FD&C BLUE NO. 1; ISOPROPYL ALCOHOL

ACTIVE INGREDIENT

Alcohol 70% v/v

PURPOSE

Antiseptic

INDICATIONS AND USAGE

- Hand sanitizer to help reduce bacteria on the skin.
- For use when soap and water are not available.